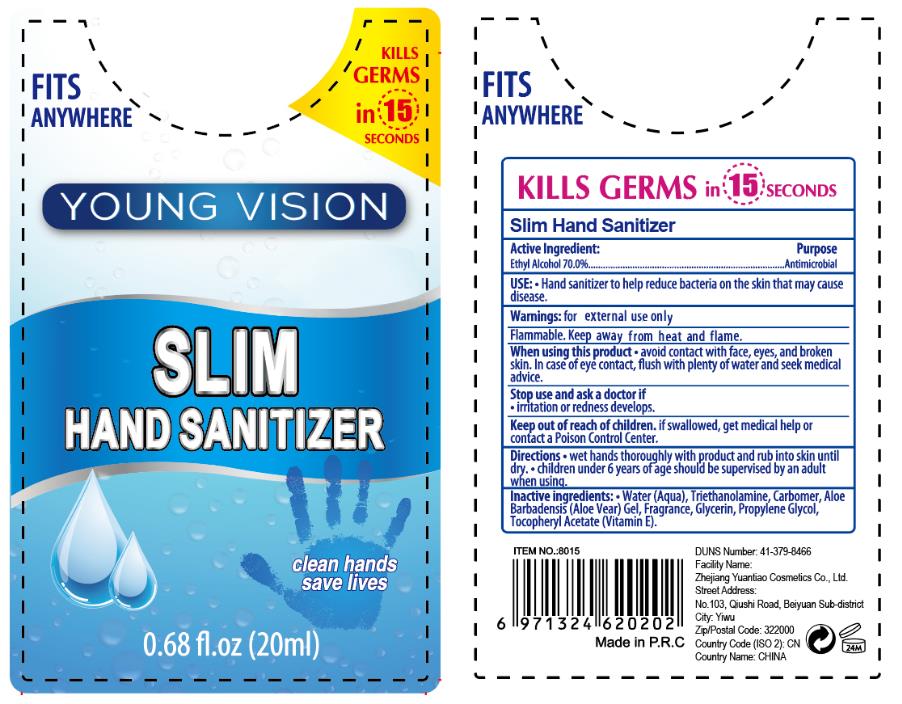 DRUG LABEL: SLIM HAND SANITIZER
NDC: 74737-2021 | Form: GEL
Manufacturer: Zhejiang Yuantiao Cosmetics Co., Ltd.
Category: otc | Type: HUMAN OTC DRUG LABEL
Date: 20200520

ACTIVE INGREDIENTS: ALCOHOL 14 mL/20 mL
INACTIVE INGREDIENTS: GLYCERIN; CARBOMER HOMOPOLYMER, UNSPECIFIED TYPE; WATER; PROPYLENE GLYCOL; ALOE VERA LEAF; .ALPHA.-TOCOPHEROL, D-

YuanTiao, Hand Sanitizer, Gel, 70% Alcohol, 20mL

Active Ingredient(s)

Ethyl Alcohol 70% v/v. Purpose: Antimicrobial

Purpose

Antimicrobial

Use

Hand sanitizer to help reduce bacteria on the skin that may cause disease.

Warnings

For external use only. Flammable. Keep away from heat or flame.

Do not use

- on children less than 2 months of age
- on open skin wounds

When using this product

- avoid contact with face, eyes, and broken skin.

In case of contact, flush with plenty of water and seek medical advice.

Stop use and ask a doctor if irritation or redness develops.

Keep out of reach of children. If swallowed, get medical help or contact a Poison Control Center.

Directions

- wet hands thoroughly with enough product and rub into skin until dry.
- children under 6 years of age should be superised by an adult when using.

Other information

Store avoid direct sunlight.

Inactive ingredients

Water (Aqua), Triethanolamine, Carbomer, Aloe Barbadensis (Aloe Vera) Gel, Fragrance, Glycerin, Propylene Glycol, Tocopheryl Acetate (Vitamin E).